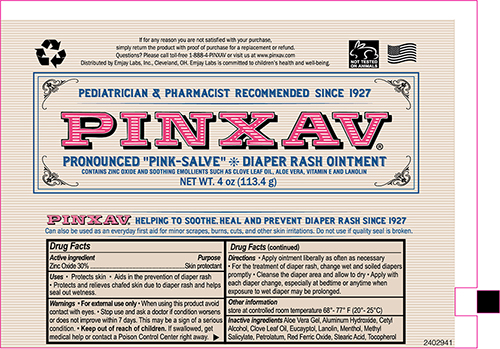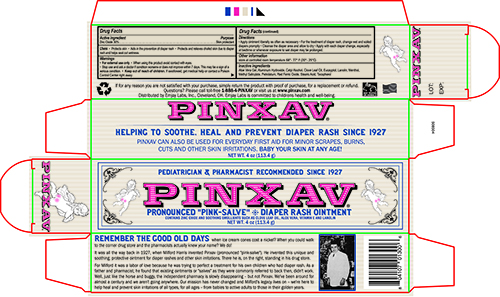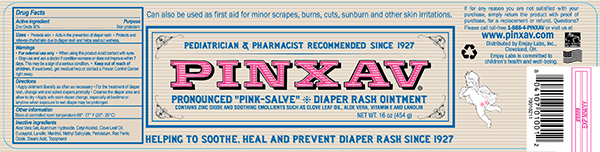 DRUG LABEL: PINXAV DAIPER RASH
NDC: 82778-342 | Form: OINTMENT
Manufacturer: Emjay Laboratories Inc.
Category: otc | Type: HUMAN OTC DRUG LABEL
Date: 20241121

ACTIVE INGREDIENTS: ZINC OXIDE 300 mg/1 g
INACTIVE INGREDIENTS: PETROLATUM; LANOLIN; STEARIC ACID; ALUMINUM HYDROXIDE; CETYL ALCOHOL; .ALPHA.-TOCOPHEROL ACETATE; METHYL SALICYLATE; EUCALYPTOL; CLOVE LEAF OIL; FERRIC OXIDE RED; ALOE VERA LEAF; MENTHOL

PINXAV DAIPER RASH OINTMENT

Drug Facts

Active ingredient

Zinc oxide 30%

Purpose

Skin Protectant

Uses

- helps treat and prevent diaper rash. Protects chafed skin due to diaper rash and helps seal out wetness.
- dries the oozing and weeping of poison ivy, poison oak and poison sumac.

Warnings

For external use only

When using this product, avoid contact with the eyes

Stop use and ask a doctor if condition worsens or does not improve within 7 days

Keep out of reach of children. If swallowed, get medical help or contact a poison control center right away.

Directions

- apply liberally as often as necessary

For diaper rash:

- change wet or soiled diapers promptly
- cleanse the diaper area and allow to dry
- apply ointment liberally, as often as necessary, with each diaper change and especially at bedtime or anytime when exposure to wet diapers may be prolonged

Inactive ingredients

Aloe Vera Gel, Aluminum Hydroxide, Cetyl Alcohol, Clove Leaf Oil, Eucayptol, Lanolin, Menthol, Methyl Salicylate, Petrolatum, Red Ferric Oxide, Stearic Acid, Tocopherol

Questions or comments?

Call 1-888-4-PINXAV or visit us at www.pinxav.com

Store at room temperature 15° - 30°C (59° - 86°F).

Principal Display Panel – Jar Label

PINXAV NDC
SKIN PROTECTANT

• helping to Soothe ,Heal and prevent Diaper rash

Net Wt 16 OZ (454 g)

Principal Display Panel - 4.0 OZ Tube

PINXAV DIAPER RASH Ointment

Skin protectant Zinc Oxide 30%

Help Soothe & Protect Chafed Skin

NET WT 4.0 OZ (113.4g)

Principal Display Panel - 4.0 OZ Carton

PINXAV DIAPER RASH Ointment

Skin protectant Zinc Oxide 30%

Help Soothe & Protect Chafed Skin

NET WT 4.0 OZ (113.4 g)